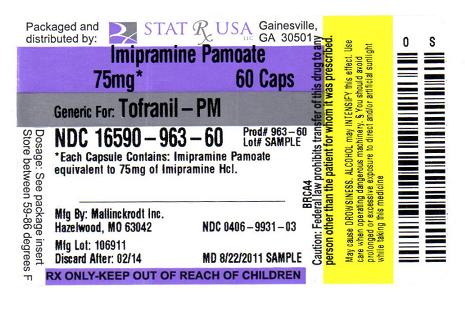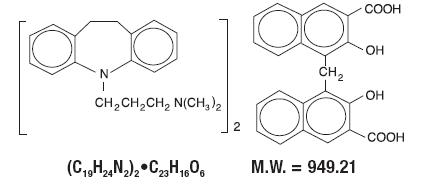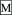 DRUG LABEL: IMIPRAMINE PAMOATE
NDC: 16590-963 | Form: CAPSULE
Manufacturer: STAT RX USA LLC
Category: prescription | Type: HUMAN PRESCRIPTION DRUG LABEL
Date: 20110825

ACTIVE INGREDIENTS: IMIPRAMINE PAMOATE 75 mg/1 1
INACTIVE INGREDIENTS: D&C RED NO. 28; FD&C BLUE NO. 1; FD&C YELLOW NO. 6; GELATIN; MAGNESIUM STEARATE; TALC; TITANIUM DIOXIDE; PROPYLPARABEN; METHYLPARABEN; STARCH, CORN

Prescribing Information

Suicidality and Antidepressant Drugs

Antidepressants increased the risk compared to placebo of suicidal thinking and behavior (suicidality) in children, adolescents, and young adults in short-term studies of major depressive disorder (MDD) and other psychiatric disorders. Anyone considering the use of imipramine pamoate or any other antidepressant in a child, adolescent, or young adult must balance this risk with the clinical need. Short-term studies did not show an increase in the risk of suicidality with antidepressants compared to placebo in adults beyond age 24; there was a reduction in risk with antidepressants compared to placebo in adults aged 65 and older. Depression and certain other psychiatric disorders are themselves associated with increases in the risk of suicide. Patients of all ages who are started on antidepressant therapy should be monitored appropriately and observed closely for clinical worsening, suicidality, or unusual changes in behavior. Families and caregivers should be advised of the need for close observation and communication with the prescriber. Imipramine pamoate is not approved for use in pediatric patients (see WARNINGS: Clinical Worsening and Suicide Risk, PRECAUTIONS: Information for Patients, and PRECAUTIONS: Pediatric Use).

DESCRIPTION

Imipramine pamoate is a tricyclic antidepressant, available as capsules for oral administration. The 75-, 100-, 125-, and 150-mg capsules contain imipramine pamoate equivalent to 75, 100, 125, and 150 mg of imipramine hydrochloride. Imipramine pamoate is 5-[3- (dimethylamino)propyl]-10, 11-dihydro-5H-dibenz[b,f]azepine 4, 4'-methylenebis- (3-hydroxy-2-naphthoate) (2:1), and its structural formula is

Imipramine pamoate is a fine, yellow, tasteless, odorless powder. It is soluble in ethanol, in acetone, in ether, in chloroform, and in carbon tetrachloride, and is insoluble in water.

Inactive Ingredients. D&C Red No. 28, FD&C Blue No. 1, FD&C Yellow No. 6, D&C Yellow No. 10 (100 mg and 125 mg capsules only), gelatin, magnesium stearate, parabens, starch, talc, and titanium dioxide.

CLINICAL PHARMACOLOGY

The mechanism of action of imipramine is not definitely known. However, it does not act primarily by stimulation of the central nervous system. The clinical effect is hypothesized as being due to potentiation of adrenergic synapses by blocking uptake of norepinephrine at nerve endings.

INDICATIONS AND USAGE

For the relief of symptoms of depression. Endogenous depression is more likely to be alleviated than other depressive states. One to three weeks of treatment may be needed before optimal therapeutic effects are evident.

CONTRAINDICATIONS

The concomitant use of monoamine oxidase inhibiting compounds is contraindicated. Hyperpyretic crises or severe convulsive seizures may occur in patients receiving such combinations. The potentiation of adverse effects can be serious, or even fatal. When it is desired to substitute imipramine pamoate capsules in patients receiving a monoamine oxidase inhibitor, as long an interval should elapse as the clinical situation will allow, with a minimum of 14 days. Initial dosage should be low and increases should be gradual and cautiously prescribed.

The drug is contraindicated during the acute recovery period after a myocardial infarction. Patients with a known hypersensitivity to this compound should not be given the drug. The possibility of cross-sensitivity to other dibenzazepine compounds should be kept in mind.

WARNINGS

Clinical Worsening and Suicide Risk

Patients with major depressive disorder (MDD), both adult and pediatric, may experience worsening of their depression and/or the emergence of suicidal ideation and behavior (suicidality) or unusual changes in behavior, whether or not they are taking antidepressant medications, and this risk may persist until significant remission occurs. Suicide is a known risk of depression and certain other psychiatric disorders, and these disorders themselves are the strongest predictors of suicide. There has been a long-standing concern, however, that antidepressants may have a role in inducing worsening of depression and the emergence of suicidality in certain patients during the early phases of treatment. Pooled analyses of short-term placebo-controlled trials of antidepressant drugs (SSRIs and others) showed that these drugs increase the risk of suicidal thinking and behavior (suicidality) in children, adolescents, and young adults (ages 18-24) with major depressive disorder (MDD) and other psychiatric disorders. Short-term studies did not show an increase in the risk of suicidality with antidepressants compared to placebo in adults beyond age 24; there was a reduction with antidepressants compared to placebo in adults aged 65 and older.

The pooled analyses of placebo-controlled trials in children and adolescents with MDD, obsessive compulsive disorder (OCD), or other psychiatric disorders included a total of 24 short-term trials of 9 antidepressant drugs in over 4400 patients. The pooled analyses of placebo-controlled trials in adults with MDD or other psychiatric disorders included a total of 295 short-term trials (median duration of 2 months) of 11 antidepressant drugs in over 77,000 patients. There was considerable variation in risk of suicidality among drugs, but a tendency toward an increase in the younger patients for almost all drugs studied. There were differences in absolute risk of suicidality across the different indications, with the highest incidence in MDD. The risk differences (drug vs placebo), however, were relatively stable within age strata and across indications. These risk differences (drug-placebo difference in the number of cases of suicidality per 1000 patients treated) are provided in Table 1.

Table 1
Age Range | Drug-Placebo Difference in Number of Cases of Suicidality per 1000 Patients Treated
Increases Compared to Placebo
<18 | 14 additional cases
18-24 | 5 additional cases
Decreases Compared to Placebo
25-64 | 1 fewer case
≥65 | 6 fewer cases

No suicides occurred in any of the pediatric trials. There were suicides in the adult trials, but the number was not sufficient to reach any conclusion about drug effect on suicide.

It is unknown whether the suicidality risk extends to longer-term use, i.e., beyond several months. However, there is substantial evidence from placebo-controlled maintenance trials in adults with depression that the use of antidepressants can delay the recurrence of depression.

All patients being treated with antidepressants for any indication should be monitored appropriately and observed closely for clinical worsening, suicidality, and unusual changes in behavior, especially during the initial few months of a course of drug therapy, or at times of dose changes, either increases or decreases.

The following symptoms, anxiety, agitation, panic attacks, insomnia, irritability, hostility, aggressiveness, impulsivity, akathisia (psychomotor restlessness), hypomania, and mania, have been reported in adult and pediatric patients being treated with antidepressants for major depressive disorder as well as for other indications, both psychiatric and nonpsychiatric. Although a causal link between the emergence of such symptoms and either the worsening of depression and/or the emergence of suicidal impulses has not been established, there is concern that such symptoms may represent precursors to emerging suicidality.

Consideration should be given to changing the therapeutic regimen, including possibly discontinuing the medication, in patients whose depression is persistently worse, or who are experiencing emergent suicidality or symptoms that might be precursors to worsening depression or suicidality, especially if these symptoms are severe, abrupt in onset, or were not part of the patient's presenting symptoms.

Families and caregivers of patients being treated with antidepressants for major depressive disorder or other indications, both psychiatric and nonpsychiatric, should be alerted about the need to monitor patients for the emergence of agitation, irritability, unusual changes in behavior, and the other symptoms described above, as well as the emergence of suicidality, and to report such symptoms immediately to health care providers. Such monitoring should include daily observation by families and caregivers. Prescriptions for imipramine pamoate should be written for the smallest quantity of capsules consistent with good patient management, in order to reduce the risk of overdose.

Screening Patients for Bipolar Disorder – A major depressive episode may be the initial presentation of bipolar disorder. It is generally believed (though not established in controlled trials) that treating such an episode with an antidepressant alone may increase the likelihood of precipitation of a mixed/manic episode in patients at risk for bipolar disorder. Whether any of the symptoms described above represent such a conversion is unknown. However, prior to initiating treatment with an antidepressant, patients with depressive symptoms should be adequately screened to determine if they are at risk for bipolar disorder; such screening should include a detailed psychiatric history, including a family history of suicide, bipolar disorder, and depression. It should be noted that imipramine pamoate is not approved for use in treating bipolar depression.

Extreme caution should be used when this drug is given to patients with cardiovascular disease because of the possibility of conduction defects, arrhythmias, congestive heart failure, myocardial infarction, strokes, and tachycardia. These patients require cardiac surveillance at all dosage levels of the drug; patients with increased intraocular pressure, history of urinary retention, or history of narrow-angle glaucoma because of the drug's anticholinergic properties; hyperthyroid patients or those on thyroid medication because of the possibility of cardiovascular toxicity; patients with a history of seizure disorder because this drug has been shown to lower the seizure threshold; patients receiving guanethidine, clonidine, or similar agents, since imipramine pamoate may block the pharmacologic effects of these drugs; patients receiving methylphenidate hydrochloride. Since methylphenidate hydrochloride may inhibit the metabolism of imipramine pamoate, downward dosage adjustment of imipramine pamoate may be required when given concomitantly with methylphenidate hydrochloride.

Since imipramine pamoate may impair the mental and/or physical abilities required for the performance of potentially hazardous tasks, such as operating an automobile or machinery, the patient should be cautioned accordingly.

Imipramine pamoate capsules may enhance the CNS depressant effects of alcohol. Therefore, it should be borne in mind that the dangers inherent in a suicide attempt or accidental overdosage with the drug may be increased for the patient who uses excessive amounts of alcohol. (See PRECAUTIONS.)

PRECAUTIONS

General

An ECG recording should be taken prior to the initiation of larger-than-usual doses of imipramine pamoate and at appropriate intervals thereafter until steady state is achieved. (Patients with any evidence of cardiovascular disease require cardiac surveillance at all dosage levels of the drug. See WARNINGS.) Elderly patients and patients with cardiac disease or a prior history of cardiac disease are at special risk of developing the cardiac abnormalities associated with the use of imipramine pamoate. It should be kept in mind that the possibility of suicide in seriously depressed patients is inherent in the illness and may persist until significant remission occurs. Such patients should be carefully supervised during the early phase of treatment with imipramine pamoate and may require hospitalization. Prescriptions should be written for the smallest amount feasible.

Hypomanic or manic episodes may occur, particularly in patients with cyclic disorders. Such reactions may necessitate discontinuation of the drug. If needed, imipramine pamoate may be resumed in lower dosage when these episodes are relieved. Administration of a tranquilizer may be useful in controlling such episodes.

An activation of the psychosis may occasionally be observed in schizophrenic patients and may require reduction of dosage and the addition of a phenothiazine.

Concurrent administration of imipramine pamoate with electroshock therapy may increase the hazards: such treatment should be limited to those patients for whom it is essential, since there is limited clinical experience.

Patients taking imipramine pamoate should avoid excessive exposure to sunlight since there have been reports of photosensitization.

Both elevation and lowering of blood sugar levels have been reported with imipramine pamoate use.

Imipramine pamoate should be used with caution in patients with significantly impaired renal or hepatic function.

Patients who develop a fever and a sore throat during therapy with imipramine pamoate should have leukocyte and differential blood counts performed.

Imipramine pamoate should be discontinued if there is evidence of pathological neutrophil depression.

Prior to elective surgery, imipramine pamoate should be discontinued for as long as the clinical situation will allow.

Information for Patients

Prescribers or other health professionals should inform patients, their families, and their caregivers about the benefits and risks associated with treatment with imipramine pamoate and should counsel them in its appropriate use. A patient Medication Guide about “Antidepressant Medicines, Depression and other Serious Mental Illness, and Suicidal Thoughts or Actions” is available for imipramine pamoate. The prescriber or health professional should instruct patients, their families, and their caregivers to read the Medication Guide and should assist them in understanding its contents. Patients should be given the opportunity to discuss the contents of the Medication Guide and to obtain answers to any questions they may have. The complete text of the Medication Guide is reprinted at the end of this document.

Patients should be advised of the following issues and asked to alert their prescriber if these occur while taking imipramine pamoate.

Clinical Worsening and Suicide Risk – Patients, their families, and their caregivers should be encouraged to be alert to the emergence of anxiety, agitation, panic attacks, insomnia, irritability, hostility, aggressiveness, impulsivity, akathisia (psychomotor restlessness), hypomania, mania, other unusual changes in behavior, worsening of depression, and suicidal ideation, especially early during antidepressant treatment and when the dose is adjusted up or down. Families and caregivers of patients should be advised to look for the emergence of such symptoms on a day-to-day basis, since changes may be abrupt. Such symptoms should be reported to the patient's prescriber or health professional, especially if they are severe, abrupt in onset, or were not part of the patient's presenting symptoms. Symptoms such as these may be associated with an increased risk for suicidal thinking and behavior and indicate a need for very close monitoring and possibly changes in the medication.

Drug Interactions

Drugs Metabolized by P450 2D6 – The biochemical activity of the drug metabolizing isozyme cytochrome P450 2D6 (debrisoquin hydroxylase) is reduced in a subset of the Caucasian population (about 7% to 10% of Caucasians are so-called “poor metabolizers”); reliable estimates of the prevalence of reduced P450 2D6 isozyme activity among Asian, African, and other populations are not yet available. Poor metabolizers have higher than expected plasma concentrations of tricyclic antidepressants (TCAs) when given usual doses. Depending on the fraction of drug metabolized by P450 2D6, the increase in plasma concentration may be small, or quite large (8-fold increase in plasma AUC of the TCA).

In addition, certain drugs inhibit the activity of this isozyme and make normal metabolizers resemble poor metabolizers. An individual who is stable on a given dose of TCA may become abruptly toxic when given one of these inhibiting drugs as concomitant therapy. The drugs that inhibit cytochrome P450 2D6 include some that are not metabolized by the enzyme (quinidine; cimetidine) and many that are substrates for P450 2D6 (many other antidepressants, phenothiazines, and the Type 1C antiarrhythmics propafenone and flecainide). While all the selective serotonin reuptake inhibitors (SSRIs), e.g., fluoxetine, sertraline, and paroxetine, inhibit P450 2D6, they may vary in the extent of inhibition. The extent to which SSRI-TCA interactions may pose clinical problems will depend on the degree of inhibition and the pharmacokinetics of the SSRI involved. Nevertheless, caution is indicated in the co-administration of TCAs with any of the SSRIs and also in switching from one class to the other. Of particular importance, sufficient time must elapse before initiating TCA treatment in a patient being withdrawn from fluoxetine, given the long half-life of the parent and active metabolite (at least 5 weeks may be necessary).

Concomitant use of tricyclic antidepressants with drugs that can inhibit cytochrome P450 2D6 may require lower doses than usually prescribed for either the tricyclic antidepressant or the other drug. Furthermore, whenever one of these other drugs is withdrawn from co-therapy, an increased dose of tricyclic antidepressant may be required. It is desirable to monitor TCA plasma levels whenever a TCA is going to be co-administered with another drug known to be an inhibitor of P450 2D6.

The plasma concentration of imipramine may increase when the drug is given concomitantly with hepatic enzyme inhibitors (e.g., cimetidine, fluoxetine) and decrease by concomitant administration with hepatic enzyme inducers (e.g., barbiturates, phenytoin), and adjustment of the dosage of imipramine may therefore be necessary.

In occasional susceptible patients or in those receiving anticholinergic drugs (including antiparkinsonism agents) in addition, the atropine-like effects may become more pronounced (e.g., paralytic ileus). Close supervision and careful adjustment of dosage is required when imipramine pamoate is administered concomitantly with anticholinergic drugs.

Avoid the use of preparations, such as decongestants and local anesthetics, that contain any sympathomimetic amine (e.g., epinephrine, norepinephrine), since it has been reported that tricyclic antidepressants can potentiate the effects of catecholamines.

Caution should be exercised when imipramine pamoate is used with agents that lower blood pressure. Imipramine pamoate may potentiate the effects of CNS depressant drugs.

Patients should be warned that imipramine pamoate may enhance the CNS depressant effects of alcohol. (See WARNINGS.)

Pregnancy

Animal reproduction studies have yielded inconclusive results. (See also ANIMAL PHARMACOLOGY & TOXICOLOGY.)

There have been no well-controlled studies conducted with pregnant women to determine the effect of imipramine on the fetus. However, there have been clinical reports of congenital malformations associated with the use of the drug. Although a causal relationship between these effects and the drug could not be established, the possibility of fetal risk from the maternal ingestion of imipramine cannot be excluded. Therefore, imipramine should be used in women who are or might become pregnant only if the clinical condition clearly justifies potential risk to the fetus.

Nursing Mothers

Limited data suggest that imipramine is likely to be excreted in human breast milk. As a general rule, a woman taking a drug should not nurse since the possibility exists that the drug may be excreted in breast milk and be harmful to the child.

Pediatric Use

Safety and effectiveness in the pediatric population have not been established (see BOX WARNING and WARNINGS-Clinical Worsening and Suicide Risk).

It is generally recommended that imipramine pamoate capsules should not be used in children because of the increased potential for acute overdosage due to the high unit potency (75 mg, 100 mg, 125 mg, and 150 mg). Each capsule contains imipramine pamoate equivalent to 75 mg, 100 mg, 125 mg, or 150 mg imipramine hydrochloride. Anyone considering the use of imipramine pamoate in a child or adolescent must balance the potential risks with the clinical need.

Geriatric Use

In the literature, there were four well-controlled, randomized, double-blind, parallel group comparison clinical studies done with Tofranil™, brand of imipramine hydrochloride tablets, in the elderly population. There was a total number of 651 subjects included in these studies. These studies did not provide a comparison to younger subjects. There were no additional adverse experiences identified in the elderly.

Clinical studies of Tofranil™, brand of imipramine hydrochloride tablets, in the original application did not include sufficient numbers of subjects aged 65 and over to determine whether they respond differently from younger subjects. Post-marketing clinical experience has not identified differences in responses between the elderly and younger subjects. In general, dose selection for the elderly should be cautious, usually starting at the low end of the dosing range, reflecting greater frequency of decreased hepatic, renal, or cardiac function, and of concomitant disease or other drug therapy.

(see also DOSAGE AND ADMINISTRATION in Adolescent and Geriatric Patients)

(see also PRECAUTIONS General)

ADVERSE REACTIONS

Note: Although the listing which follows includes a few adverse reactions which have not been reported with this specific drug, the pharmacological similarities among the tricyclic antidepressant drugs require that each of the reactions be considered when imipramine is administered.

Cardiovascular: Orthostatic hypotension, hypertension, tachycardia, palpitation, myocardial infarction, arrhythmias, heart block, ECG changes, precipitation of congestive heart failure, stroke.

Psychiatric: Confusional states (especially in the elderly) with hallucinations, disorientation, delusions; anxiety, restlessness, agitation; insomnia and nightmares; hypomania; exacerbation of psychosis.

Neurological: Numbness, tingling, paresthesias of extremities; incoordination, ataxia, tremors; peripheral neuropathy; extrapyramidal symptoms; seizures, alterations in EEG patterns; tinnitus.

Anticholinergic: Dry mouth, and, rarely, associated sublingual adenitis; blurred vision, disturbances of accommodation, mydriasis; constipation, paralytic ileus; urinary retention, delayed micturition, dilation of the urinary tract.

Allergic: Skin rash, petechiae, urticaria, itching, photosensitization; edema (general or of face and tongue); drug fever; cross-sensitivity with desipramine.

Hematologic: Bone marrow depression including agranulocytosis; eosinophilia; purpura; thrombocytopenia.

Gastrointestinal: Nausea and vomiting, anorexia, epigastric distress, diarrhea; peculiar taste, stomatitis, abdominal cramps, black tongue.

Endocrine: Gynecomastia in the male; breast enlargement and galactorrhea in the female; increased or decreased libido, impotence; testicular swelling; elevation or depression of blood sugar levels; inappropriate antidiuretic hormone (ADH) secretion syndrome.

Other: Jaundice (simulating obstructive); altered liver function; weight gain or loss; perspiration; flushing; urinary frequency; drowsiness, dizziness, weakness and fatigue; headache; parotid swelling; alopecia; proneness to falling.

Withdrawal Symptoms: Though not indicative of addiction, abrupt cessation of treatment after prolonged therapy may produce nausea, headache and malaise.

OVERDOSAGE

Deaths may occur from overdosage with this class of drugs. Multiple drug ingestion (including alcohol) is common in deliberate tricyclic overdose. As the management is complex and changing, it is recommended that the physician contact a poison control center for current information on treatment. Signs and symptoms of toxicity develop rapidly after tricyclic overdose. Therefore, hospital monitoring is required as soon as possible.

Children have been reported to be more sensitive than adults to an acute overdosage of imipramine pamoate. An acute overdose of any amount in infants or young children, especially, must be considered serious and potentially fatal.

Manifestations

These may vary in severity depending upon factors such as the amount of drug absorbed, the age of the patient, and the interval between drug ingestion and the start of treatment. Critical manifestations of overdose include cardiac dysrhythmias, severe hypotension, convulsions, and CNS depression including coma. Changes in the electrocardiogram, particularly in QRS axis or width, are clinically significant indicators of tricyclic toxicity.

Other CNS manifestations may include drowsiness, stupor, ataxia, restlessness, agitation, hyperactive reflexes, muscle rigidity, athetoid and choreiform movements.

Cardiac abnormalities may include tachycardia, and signs of congestive failure. Respiratory depression, cyanosis, shock, vomiting, hyperpyrexia, mydriasis, and diaphoresis may also be present.

Management

Obtain an ECG and immediately initiate cardiac monitoring. Protect the patient's airway, establish an intravenous line, and initiate gastric decontamination. A minimum of 6 hours of observation with cardiac monitoring and observation for signs of CNS or respiratory depression, hypotension, cardiac dysrhythmias and/or conduction blocks, and seizures is necessary. If signs of toxicity occur at any time during this period, extended monitoring is required. There are case reports of patients succumbing to fatal dysrhythmias late after overdose; these patients had clinical evidence of significant poisoning prior to death and most received inadequate gastrointestinal decontamination. Monitoring of plasma drug levels should not guide management of the patient.

Gastrointestinal Decontamination – All patients suspected of tricyclic overdose should receive gastrointestinal decontamination. This should include large volume gastric lavage followed by activated charcoal. If consciousness is impaired, the airway should be secured prior to lavage. Emesis is contraindicated.

Cardiovascular – A maximal limb-lead QRS duration of ≥ 0.10 seconds may be the best indication of the severity of the overdose. Intravenous sodium bicarbonate should be used to maintain the serum pH in the range of 7.45 to 7.55. If the pH response is inadequate, hyperventilation may also be used. Concomitant use of hyperventilation and sodium bicarbonate should be done with extreme caution, with frequent pH monitoring. A pH >7.60 or a pCO2 < 20 mmHg is undesirable.

Dysrhythmias unresponsive to sodium bicarbonate therapy/hyperventilation may respond to lidocaine, bretylium, or phenytoin. Type 1A and 1C antiarrhythmics are generally contraindicated (e.g., quinidine, disopyramide, and procainamide).

In rare instances, hemoperfusion may be beneficial in acute refractory cardiovascular instability in patients with acute toxicity. However, hemodialysis, peritoneal dialysis, exchange transfusions, and forced diuresis generally have been reported as ineffective in tricyclic poisoning.

CNS – In patients with CNS depression, early intubation is advised because of the potential for abrupt deterioration. Seizures should be controlled with benzodiazepines, or if these are ineffective, other anticonvulsants (e.g., phenobarbital, phenytoin). Physostigmine is not recommended except to treat life-threatening symptoms that have been unresponsive to other therapies, and then only in consultation with a poison control center.

Psychiatric Follow-up – Since overdosage is often deliberate, patients may attempt suicide by other means during the recovery phase. Psychiatric referral may be appropriate.

Pediatric Management – The principles of management of child and adult overdosages are similar. It is strongly recommended that the physician contact the local poison control center for specific pediatric treatment.

DOSAGE AND ADMINISTRATION

The following recommended dosages for imipramine pamoate capsules should be modified as necessary by the clinical response and any evidence of intolerance.

Initial Adult Dosage

Outpatients – Therapy should be initiated at 75 mg/day. Dosage may be increased to 150 mg/day which is the dose level at which optimum response is usually obtained. If necessary, dosage may be increased to 200 mg/day.

Dosage higher than 75 mg/day may also be administered on a once-a-day basis after the optimum dosage and tolerance have been determined. The daily dosage may be given at bedtime. In some patients it may be necessary to employ a divided-dose schedule.

As with all tricyclics, the antidepressant effect of imipramine may not be evident for one to three weeks in some patients.

Hospitalized Patients – Therapy should be initiated at 100 to 150 mg/day and may be increased to 200 mg/day. If there is no response after two weeks, dosage should be increased to 250 to 300 mg/day.

Dosage higher than 150 mg/day may also be administered on a once-a-day basis after the optimum dosage and tolerance have been determined. The daily dosage may be given at bedtime. In some patients it may be necessary to employ a divided-dose schedule.

As with all tricyclics, the antidepressant effect of imipramine may not be evident for one to three weeks in some patients.

Adult Maintenance Dosage – Following remission, maintenance medication may be required for a longer period of time at the lowest dose that will maintain remission after which the dosage should gradually be decreased.

The usual maintenance dosage is 75 to 150 mg/day. The total daily dosage can be administered on a once-a-day basis, preferably at bedtime. In some patients it may be necessary to employ a divided-dose schedule.

In cases of relapse due to premature withdrawal of the drug, the effective dosage of imipramine should be reinstituted.

Adolescent and Geriatric Patients – Therapy in these age groups should be initiated with Tofranil™, brand of imipramine hydrochloride tablets, at a total daily dosage of 25 to 50 mg, since imipramine pamoate capsules are not available in these strengths. Dosage may be increased according to response and tolerance, but it is generally unnecessary to exceed 100 mg/day in these patients. Imipramine pamoate capsules may be used when total daily dosage is established at 75 mg or higher.

The total daily dosage can be administered on a once-a-day basis, preferably at bedtime. In some patients it may be necessary to employ a divided-dose schedule.

As with all tricyclics, the antidepressant effect of imipramine may not be evident for one to three weeks in some patients.

Adolescent and geriatric patients can usually be maintained at lower dosage. Following remission, maintenance medication may be required for a longer period of time at the lowest dose that will maintain remission after which the dosage should gradually be decreased.

The total daily maintenance dosage can be administered on a once-a-day basis, preferably at bedtime. In some patients it may be necessary to employ a divided-dose schedule.

In cases of relapse due to premature withdrawal of the drug, the effective dosage of imipramine should be reinstituted.

HOW SUPPLIED Imipramine Pamoate Capsules

Capsules 75 mg - coral body imprinted in black “ ” and coral cap imprinted in black “75”.

Bottles of 30............................................NDC 0406-9931-03

Capsules 100 mg - maize body imprinted in black “ ” and coral cap imprinted in black “100”.

Bottles of 30...........................................NDC 0406-9932-03

Capsules 125 mg - ivory body imprinted in black “ ” and coral cap imprinted in black “125”.

Bottles of 30...........................................NDC 0406-9933-03

Capsules 150 mg - coral body imprinted in black “ ” and coral cap imprinted in black “150”.

Bottles of 30...........................................NDC 0406-9934-03

Store at 20° to 25°C (68° to 77°F) [see USP Controlled Room Temperature].

Dispense in tight container (USP) with a child-resistant closure.

ANIMAL PHARMACOLOGY & TOXICOLOGY

A. Acute: Oral LD50:

Mouse 2185 mg/kg

Rat (F) 1142 mg/kg

(M) 1807 mg/kg

Rabbit 1016 mg/kg

Dog 693 mg/kg (Emesis ED50)

B. Subacute:

Two three-month studies in dogs gave evidence of an adverse drug effect on the testes, but only at the highest dose level employed, i.e., 90 mg/kg (10 times the maximum human dose). Depending on the histological section of the testes examined, the findings consisted of a range of degenerative changes up to and including complete atrophy of the seminiferous tubules, with spermatogenesis usually arrested.

Human studies show no definitive effect on sperm count, sperm motility, sperm morphology or volume of ejaculate.

Rat

One three-month study was done in rats at dosage levels comparable to those of the dog studies. No adverse drug effect on the testes was noted in this study, as confirmed by histological examination.

C. Reproduction/Teratogenic:

Oral: Imipramine pamoate was fed to male and female albino rats for 28 weeks through two breeding cycles at dose levels of 15 mg/kg/day and 40 mg/kg/day (equivalent to 2 1/2 and 7 times the maximum human dose).

No abnormalities which could be related to drug administration were noted in gross inspection. Autopsies performed on pups from the second breeding likewise revealed no pathological changes in organs or tissues; however, a decrease in mean litter size from both matings was noted in the drug-treated groups and significant growth suppression occurred in the nursing pups of both sexes in the high group as well as in the females of the low-level group. Finally, the lactation index (pups weaned divided by number left to nurse) was significantly lower in the second litter of the high-level group.

Tofranil and are trademarks of Mallinckrodt Inc.

Manufactured by
Patheon Inc.
Whitby, Ontario, Canada
L1N 5Z5

Manufactured for
Mallinckrodt Inc.
Hazelwood, MO 63042 USA

MEDICATION GUIDE

Antidepressant Medicines, Depression and other Serious Mental Illnesses,
and Suicidal Thoughts or Actions

Read the Medication Guide that comes with you or your family member's antidepressant medicine. This Medication Guide is only about the risk of suicidal thoughts and actions with antidepressant medicines. Talk to your, or your family member's, healthcare provider about:

- all risks and benefits of treatment with antidepressant medicines
- all treatment choices for depression or other serious mental illness

What is the most important information I should know about antidepressant medicines, depression and other serious mental illnesses, and suicidal thoughts or actions?

1. Antidepressant medicines may increase suicidal thoughts or actions in some children, teenagers, and young adults within the first few months of treatment.
2. Depression and other serious mental illnesses are the most important causes of suicidal thoughts and actions. Some people may have a particularly high risk of having suicidal thoughts or actions. These include people who have (or have a family history of) bipolar illness (also called manic-depressive illness) or suicidal thoughts or actions.
3. How can I watch for and try to prevent suicidal thoughts and actions in myself or a family member?

- Pay close attention to any changes, especially sudden changes, in mood, behaviors, thoughts, or feelings. This is very important when an antidepressant medicine is started or when the dose is changed.
- Call the healthcare provider right away to report new or sudden changes in mood, behavior, thoughts, or feelings.
- Keep all follow-up visits with the healthcare provider as scheduled. Call the healthcare provider between visits as needed, especially if you have concerns about symptoms.

Call a healthcare provider right away if you or your family member has any of the following symptoms, especially if they are new, worse, or worry you:

- thoughts about suicide or dying
- attempts to commit suicide
- new or worse depression
- new or worse anxiety
- feeling very agitated or restless
- panic attacks
- trouble sleeping (insomnia)

- new or worse irritability
- acting aggressive, being angry, or violent
- acting on dangerous impulses
- an extreme increase in activity and talking (mania)
- other unusual changes in behavior or mood

What else do I need to know about antidepressant medicines?

- Never stop an antidepressant medicine without first talking to a healthcare provider. Stopping an antidepressant medicine suddenly can cause other symptoms.
- Antidepressants are medicines used to treat depression and other illnesses. It is important to discuss all the risks of treating depression and also the risks of not treating it. Patients and their families or other caregivers should discuss all treatment choices with the healthcare provider, not just the use of antidepressants.
- Antidepressant medicines have other side effects. Talk to the healthcare provider about the side effects of the medicine prescribed for you or your family member.
- Antidepressant medicines can interact with other medicines. Know all of the medicines that you or your family member takes. Keep a list of all medicines to show the healthcare provider. Do not start new medicines without first checking with your healthcare provider.
- Not all antidepressant medicines prescribed for children are FDA approved for use in children. Talk to your child's healthcare provider for more information.

Call your doctor for medical advice about side effects. You may report side effects to FDA at 1-800-FDA-1088.

This Medication Guide has been approved by the U.S. Food and Drug Administration for all antidepressants.

Mallinckrodt Inc.
Hazelwood, MO 63042 USA

COVIDIEN™
Mallinckrodt

Rev 05/2009